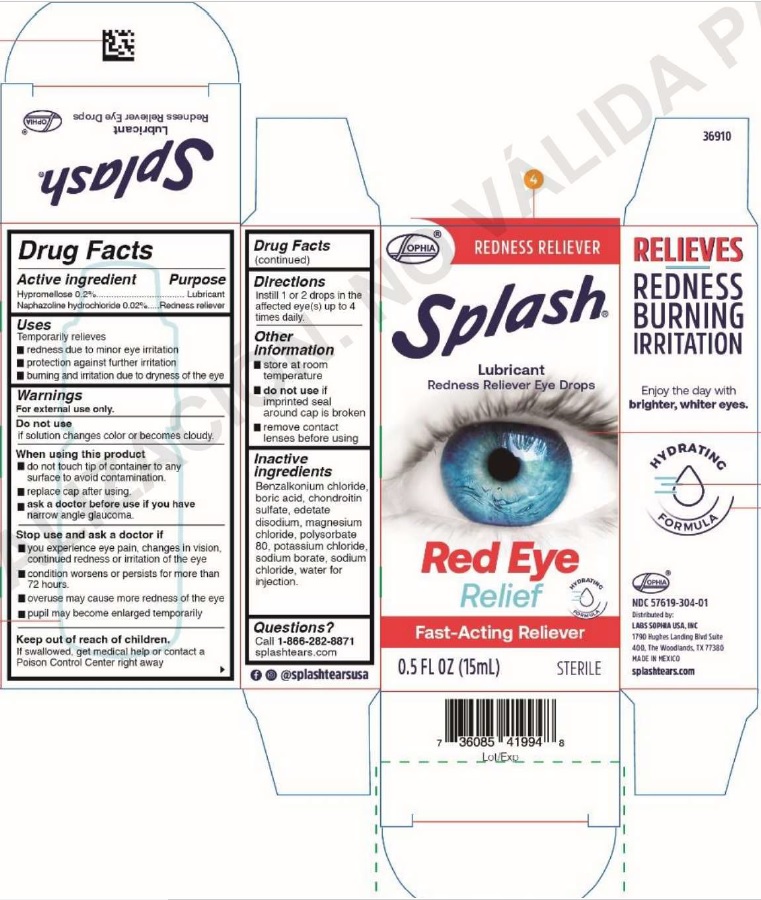 DRUG LABEL: Splash Redness Reliever
NDC: 57619-304 | Form: SOLUTION/ DROPS
Manufacturer: LABORATORIOS SOPHIA, S.A. DE C.V.
Category: otc | Type: HUMAN OTC DRUG LABEL
Date: 20250509

ACTIVE INGREDIENTS: HYPROMELLOSE 2910 (4000 MPA.S) 0.2 g/100 mL; NAPHAZOLINE HYDROCHLORIDE 0.02 g/100 mL
INACTIVE INGREDIENTS: SODIUM BORATE; POLYSORBATE 80; CHONDROITIN SULFATE (BOVINE); MAGNESIUM CHLORIDE; WATER; POTASSIUM CHLORIDE; SODIUM CHLORIDE; EDETATE DISODIUM; BENZALKONIUM CHLORIDE; BORIC ACID

Splash Redness Reliever

Active ingredient . . . . . . . . . . . . . . . . Purpose
Hypromellose 0.2%............................Lubricant
Naphazoline hydrochloride 0.02%.....Redness reliever

Purpose

Uses

Temporarily relieves

- redness due to minor eye irritation
- protection against further irritation
- burning and irritation due to dryness of the eye

Warnings

For external use only.

Do not use

if solution changes color or becomes cloudy.

When using this product

- do not touch tip of container to any surface to avoid contamination.
- replace cap after using.

ask a doctor before use if you have narrow angle glaucoma.

Stop use and ask a doctor if

- you experience eye pain, changes in vision, continued redness or irritation of the eye
- condition worsens or persists for more than 72 hours.
- overuse may cause more redness of the eye
- pupil may become enlarged temporarily

Keep out of reach of children.

If swallowed, get medical help or contat a Poison Control Center right away

Directions

Instill 1 or 2 drops in the affected eye(s) up to 4 times daily.

Other information

- store at room temperature
- do not use if imprinted seal around cap is broken
- remove contact lenses before using

Inactive ingredients

benzalkonium chloride, boric acid, chondroitin sulfate, edetate disodium, magnesium chloride, polysorbate 80, potassium chloride, sodium borate, sodium chloride, water for injection.

Questions?

Call 1-866-282-8871

splashtears.com

PACKAGE LABEL

Sophia®

REDNESS RELIEVER

Splash®
Lubricant

Redness Reliever Eye Drops

Red Eye Relief
Fast-Acting Reliever
0.5 FL OZ (15 mL)

STERILE

RELIEVES REDNESS BURNING IRRITATION

NDC 57619-304-01
Distributed by:
LABS SOPHIA USA, INC
1790 Hughes Landing Blvd, Suite 400
The Woodlands, TX 77380
MADE IN MEXICO

splashtears.com